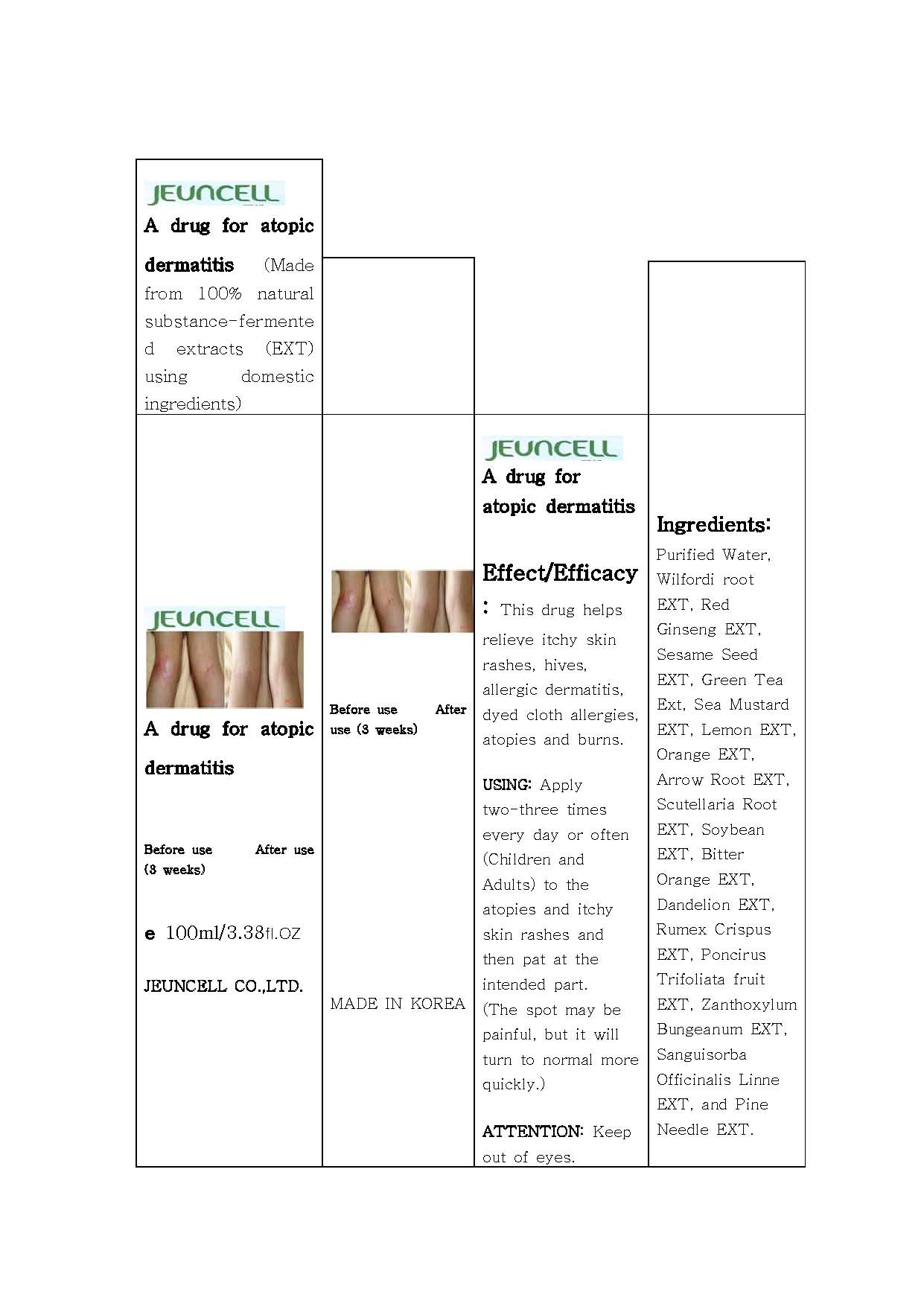 DRUG LABEL: JEUNCELL a drug for atopic dermatitis
NDC: 54296-1001 | Form: LIQUID
Manufacturer: Jeun Cell Ltd
Category: otc | Type: HUMAN OTC DRUG LABEL
Date: 20121125

ACTIVE INGREDIENTS: RUMEX CRISPUS WHOLE 5 mg/100 mL
INACTIVE INGREDIENTS: BITTER ORANGE OIL; TRIPTERYGIUM WILFORDII ROOT; ASIAN GINSENG; SESAME SEED; GREEN TEA LEAF; MUSTARD OIL; LEMON; ORANGE; SCUTELLARIA LATERIFLORA TOP; SOYBEAN; PONCIRUS TRIFOLIATA FRUIT; ZANTHOXYLUM BUNGEANUM FRUIT; SANGUISORBA OFFICINALIS LEAF; PINE NEEDLE OIL (PINUS MUGO)

Drug Facts

ACTIVE INGREDIENT

rumex crispus extract

INACTIVE INGREDIENT

wilfordi root extract, red ginseng extract, sesame seed extract, green tea extract, sea mustard extract, lemon extract, orange extract, arrow root extract, scutellaria root extract, soybean extract, dandelion extract, poncirus trifoliata fruit extract, zanthoxylum bungeanum extract, sanguisorba officinalis linne extract, pine needle extract

PURPOSE

moisturizer for atopic skin

keep out of reach of the children

INDICATIONS AND USAGE

- applied area: skin
- apply two-three times every day or often to the atopies and itchy skin rashes
- apply sufficient quantity to the intended part

When using this product
- keep out of eyes, ears, and mouth. If contact occurs, rinse with plenty of cold water right away and contact a physician. If swallowing, drink plenty of water and contact a physician

DOSAGE AND ADMINISTRATION

for external use only